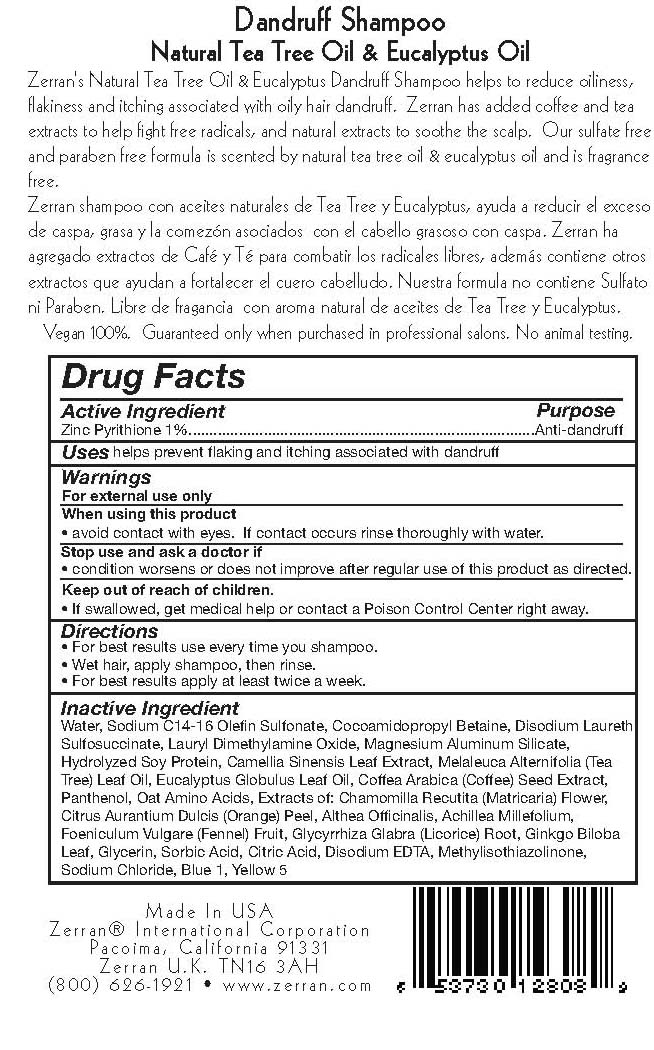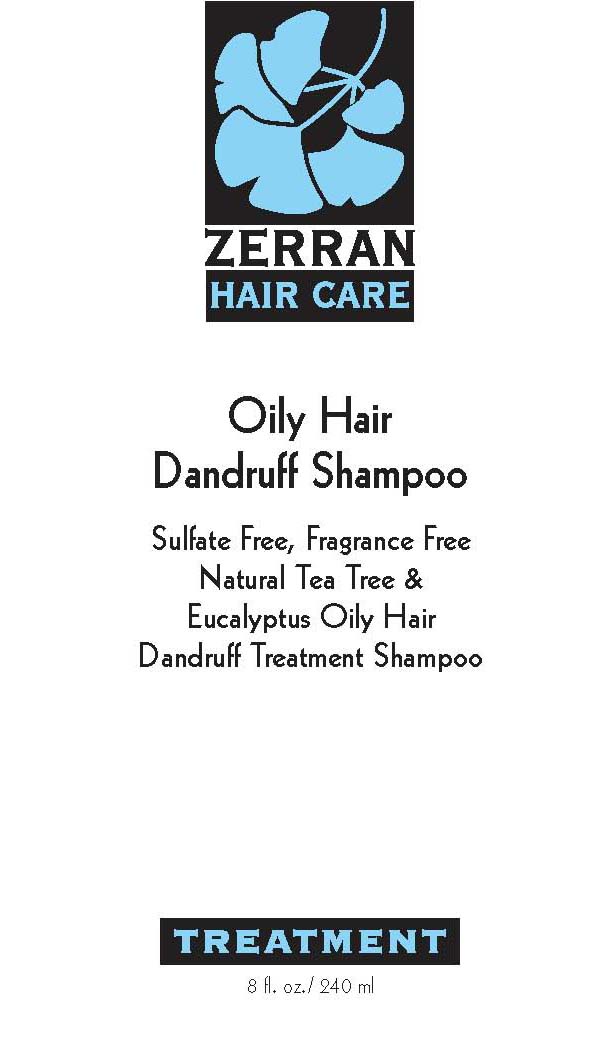 DRUG LABEL: Oily Hair Dandruff 
NDC: 38755-0111 | Form: CREAM
Manufacturer: Zerran International Corporation
Category: otc | Type: HUMAN OTC DRUG LABEL
Date: 20120126

ACTIVE INGREDIENTS: PYRITHIONE ZINC 1 mL/100 mL
INACTIVE INGREDIENTS: SODIUM C14-16 OLEFIN SULFONATE; DISODIUM LAURETH SULFOSUCCINATE; MAGNESIUM ALUMINUM SILICATE; CORYMBIA CITRIODORA LEAF OIL; ARABICA COFFEE BEAN; PANTHENOL; MATRICARIA RECUTITA; ORANGE PEEL; ACHILLEA MILLEFOLIUM; BITTER FENNEL; GLYCYRRHIZA GLABRA; GINKGO; GLYCERIN; SORBIC ACID; CITRIC ACID MONOHYDRATE; EDETATE DISODIUM; METHYLISOTHIAZOLINONE; SODIUM CHLORIDE

Oily Hair Dandruff Shampoo

ACTIVE INGREDIENT

Drug Facts Purpose
Zinc Pyrithione 1% Anti-Dandruff

PURPOSE

helps prevent flaking and itching associated with dandruff

Keep out of reach of children
-if swallowed, get medical help or contact a Poison Control Center right away.

INDICATIONS AND USAGE

-for external use only

When using this product
-avoid contact with eyes. If contact occurs rinse thoroughly with water
Stop use and ask a doctor if
-condition worsens or does not improve after regular use of this product as directed

DOSAGE AND ADMINISTRATION

-For best results use every time you shampoo.
-Wet hair, apply shampoo, then rinse.
-For best results apply at least twice a week

INACTIVE INGREDIENT

Inactive Ingredients: Water, Sodium C14-16 Olefin Sulfonate, Cocamidopropyl Betaine, Disodium Laureth Sulfosuccinate, Lauryl Dimethylamie Oxide, Magnesium Aluminum Silicate, Hydrolyzed Soy Protein, Camellia Sinensis Leaf Extract, Melaleuca Alternifolia (Tea Tree) Leaf Oil, Eucalyptus Globulus Leaf Oil, Coffea Arabica (Coffee) Seed Extract, Panthenol, Oat Amino Acids, Extracts of: Chamomilla Recutita (Matricaria) Flower, Citrus Aurantium Dulcis (Orange) Peel, Althea Officinalis, Achillea Millefolium, Foeniculum Vulgare (Fennel) Fruit, Glycyrrhiza Glabra (Licorice) Root, Ginkgo Biloba Leaf, Glycerin, Sorbic Acid, Citric Acid, Disodium EDTA, Methylisothiazolinone, Sodium Chloride, Blue 1, Yellow 5

PACKAGE LABEL

Zerran Hair Care
Oily Hair Dandruff Shampoo
33.81 fl.oz./1 Liter
8fl. oz./240 ml